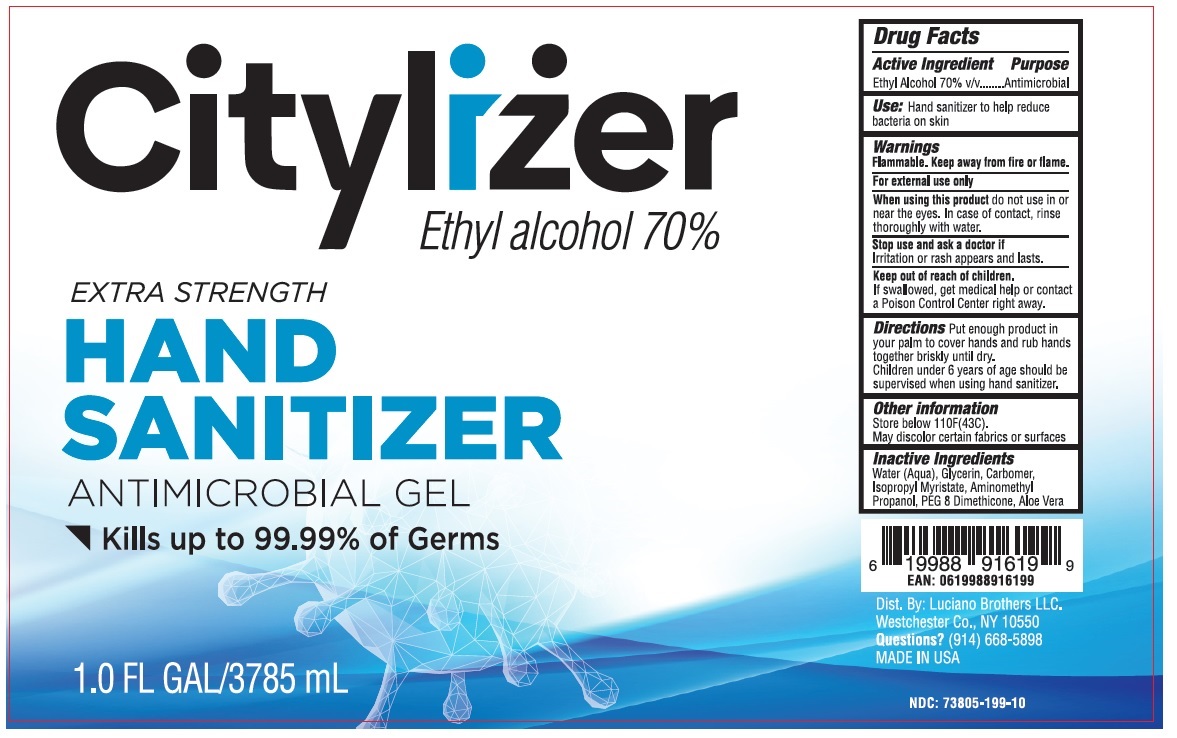 DRUG LABEL: Citylizer HAND SANITIZER ANTIMICROBIAL Gel
NDC: 73805-199 | Form: GEL
Manufacturer: Luciano Brothers LLC
Category: otc | Type: HUMAN OTC DRUG LABEL
Date: 20200321

ACTIVE INGREDIENTS: ALCOHOL 70 mL/100 mL
INACTIVE INGREDIENTS: WATER; GLYCERIN; CARBOMER HOMOPOLYMER, UNSPECIFIED TYPE; ISOPROPYL MYRISTATE; AMINOMETHYLPROPANOL; PEG-8 DIMETHICONE; ALOE VERA LEAF

Citylizer HAND SANITIZER ANTIMICROBIAL GEL

Active Ingredient

Ethyl Alcohol 70% v/v

Purpose

Antimicrobial

Use:

Hand sanitizer to help reduce bacteria on skin

Warnings

Flammable. Keep away from fire or flame.

For external use only

When using this product do not use in or near the eyes. In case of contact, rinse thoroughly with water.

Stop use and ask a doctor if Irritation or rash appears and lasts.

Keep out of reach of children.

If swallowed, get medical help or contact a Poison Control Center right away.

Directions

Put enough product in your palm to cover hands and rub hands together briskly until dry. Children under 6 years of age should be supervised when using hand sanitizer.

Other information

Store below 110F(43C). May discolor certain fabrics or surfaces

Inactive Ingredients

Water (Aqua), Glycerin, Carbomer, Isopropyl Myristate, Aminomethyl Propanol, PEG 8 Dimethicone, Aloe Vera

EXTRA STRENGTH

ANTIMICROBIAL GEL

Kills up to 99.99% of Germs

Dist. By: Luciano Brothers LLC Westchester Co., NY 10705

Questions? (914) 668-5898